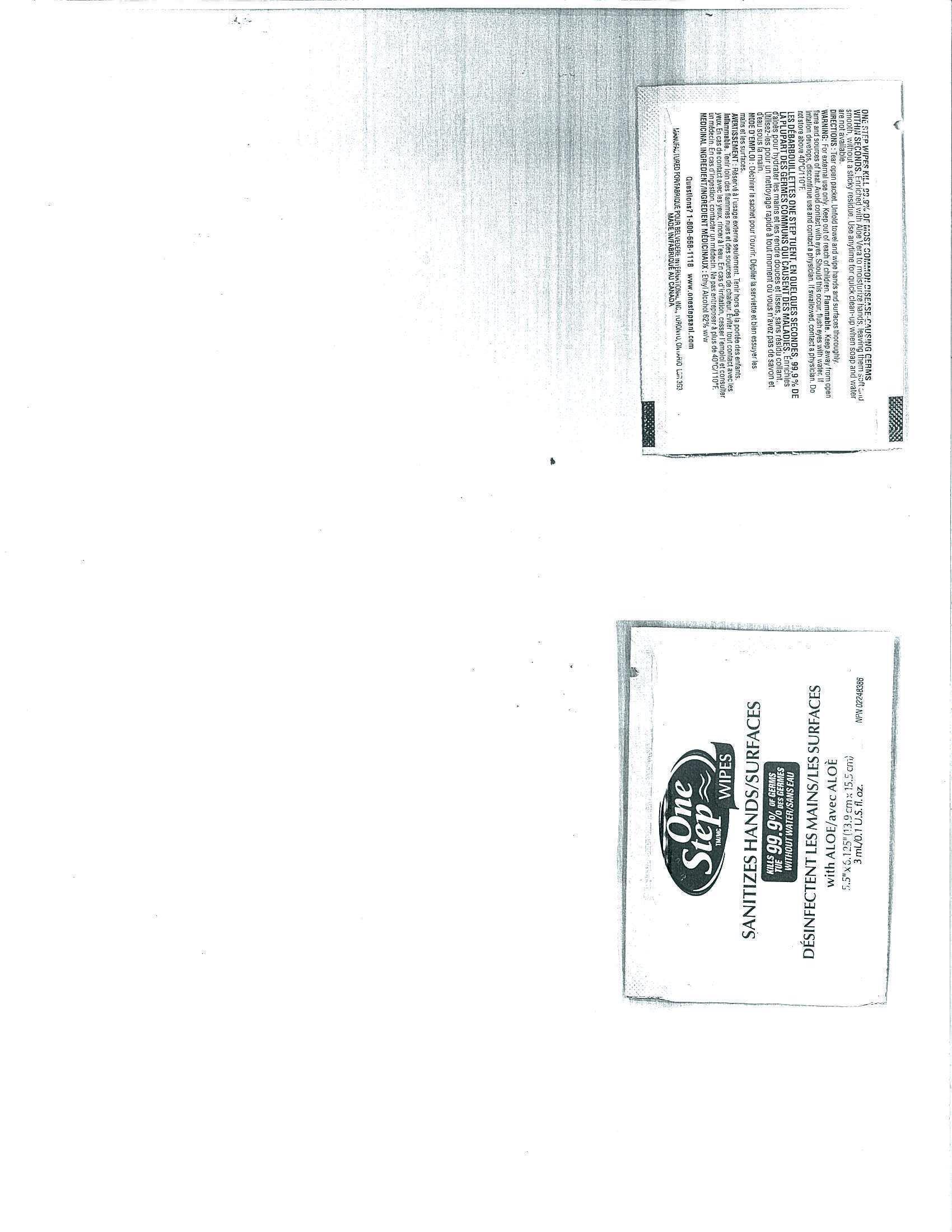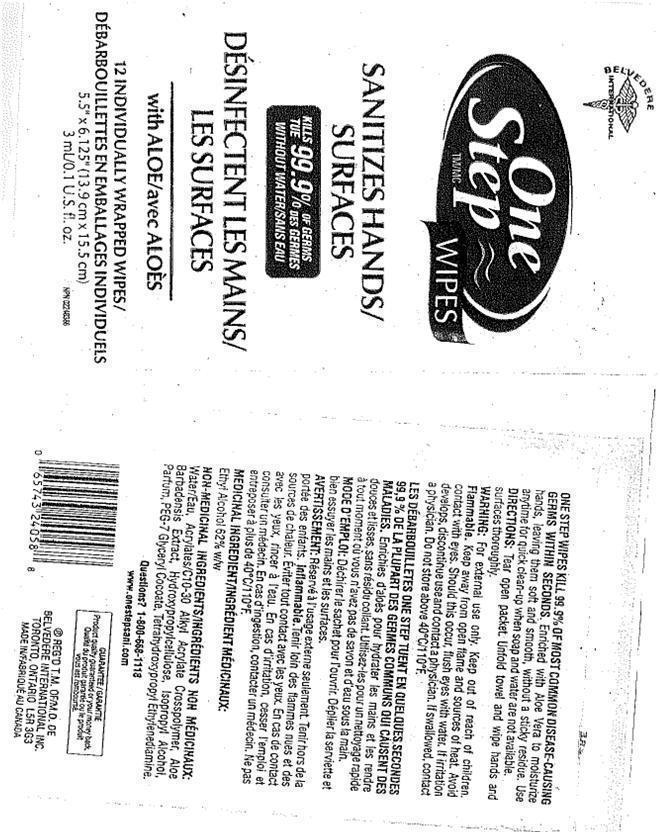 DRUG LABEL: One Step Wipes
NDC: 60742-200 | Form: LIQUID
Manufacturer: BELVEDERE INTERNATIONAL INC.
Category: otc | Type: HUMAN OTC DRUG LABEL
Date: 20181213

ACTIVE INGREDIENTS: ALCOHOL 62 mL/100 mL
INACTIVE INGREDIENTS: WATER; CARBOMER HOMOPOLYMER TYPE C (ALLYL PENTAERYTHRITOL CROSSLINKED); ALOE VERA LEAF; HYDROXYPROPYL CELLULOSE; ISOPROPYL ALCOHOL; PEG-7 GLYCERYL COCOATE

DRUG FACTS

ACTIVE INGREDIENT

ETHYL ALCOHOL 62% W/W

PURPOSE

USE ANYTIME FOR QUICK CLEAN UP WHEN SOAP AND WATER ARE NOT AVAILABLE

KEEP OUT OF REACH OF CHILDREN

INDICATIONS AND USAGE

USE ANYTIME FOR QUICK CLEAN UP WHEN SOAP AND WATER ARE NOT AVAILABLE

WARNINGS

FOR EXTERNAL USE ONLY, KEEP OUT OF REACH OF CHILDREN, FLAMMABLE, KEEP AWAY FROM OPEN FLAME AND SOURCES OF HEAT. AVOID CONTACT WITH EYES SHOULD THIS OCCUR FLUSH EYES WITH WATER. IF IRRITATION DEVELOPS, DISCONTINUE USE AND CONTACT A PHYSICIAN. IF SWALLOWED, CONTACT A PHYSICIAN. DO NOT STORE ABOVE 40^0 C/110^0F

DOSAGE AND ADMINISTRATION

TEAR OPEN PACKET. UNFOLD TOWEL AND WIPE HANDS THOROUGHLY

INACTIVE INGREDIENT

WATER, ACRYLATES/C10-30 ALKYL ACRYLATE CROSSPOLYMER, ALOE BARBADENSIS EXTRACT, HYDROXYPROPYLCELLULOSE, ISOPROPYL ALCOHOL, PARFUM, PEG-7 GLYCERYL COCOATE, TETRAHYDROXYPROPYL ETHYLENEDIAMINE.